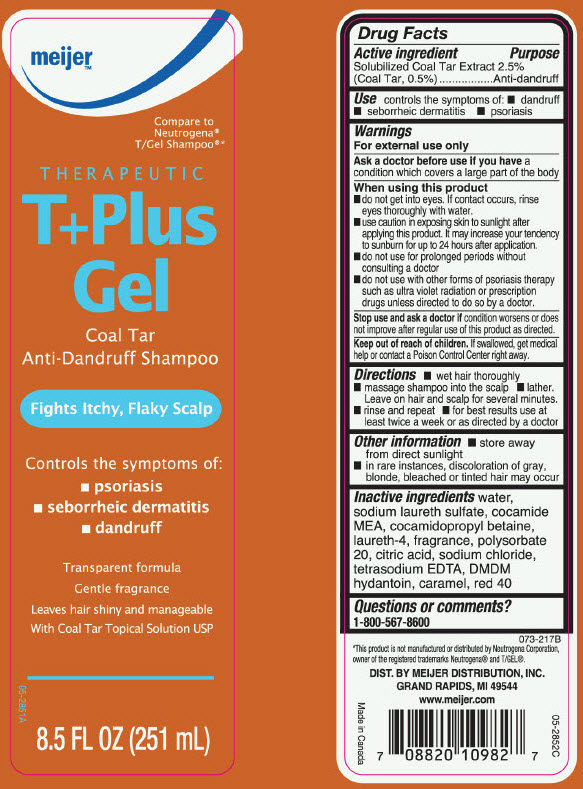 DRUG LABEL: Meijer T Plus Gel Coal Tar Anti-Dandruff
NDC: 41250-249 | Form: SHAMPOO
Manufacturer: Meijer Distribution, Inc
Category: otc | Type: HUMAN OTC DRUG LABEL
Date: 20241105

ACTIVE INGREDIENTS: Coal Tar 5 mg/1 mL
INACTIVE INGREDIENTS: Water; SODIUM LAURETH-3 SULFATE; COCO MONOETHANOLAMIDE; Cocamidopropyl Betaine; Laureth-4; Polysorbate 20; CITRIC ACID MONOHYDRATE; Sodium Chloride; EDETATE SODIUM; DMDM Hydantoin; Caramel; FD&C RED NO. 40

Meijer™ T+Plus Gel Coal Tar Anti-Dandruff Shampoo
Anti-dandruff

Drug Facts

Active ingredient

Solubilized Coal Tar Extract 2.5% (Coal Tar, 0.5%)

Purpose

Anti-dandruff

Use

controls the symptom of:

- dandruff
- seborrheic dermatitis
- psoriasis

Warnings

For external use only

ASK DOCTOR

As a doctor before use if you have a condition which covers a large part of the body

When using this product

- do not get into eyes. If contact occurs, rinse eyes thoroughly with water.
- use caution in exposing skin to sunlight after applying this product. It may increase your tendency to sunburn for up to 24 hours after application.
- do not use for prolonged periods without consulting a doctor
- do not use with other forms of psoriasis therapy such as ultra violet radiation or prescription drugs unless directed to do so by a doctor.

Stop use and ask a doctor if condition worsens or does not improve after regular use of this product as directed.

Keep out of reach of children. If swallowed, get medical help or contact a Poison Control Center right away.

Directions

- wet hair thoroughly
- massage shampoo into the scalp
- lather. Leave on hair and scalp for several minutes
- rinse and repeat
- for best results use at least twice a week or as directed by a doctor

Other information

- store away from direct sunlight
- in rare instances, discoloration of gray, blonde, bleached or tinted hair may occur

Inactive ingredients

water, sodium laureth sulfate, cocamide MEA, cocamidopropyl betaine, laureth-4, fragrance, polysorbate 20, citric acid, sodium chloride, tetrasodium EDTA, DMDM hydantoin, caramel, red 40

Questions or comments?

1-800-567-8600

DIST. BY MEIJER DISTRIBUTION, INC.
GRAND RAPIDS, MI 49544

PRINCIPAL DISPLAY PANEL - 251 mL Bottle Label

meijer™

Compare to
Neutrogena®
T/Gel Shampoo®*

THERAPEUTIC
T+Plus
Gel

Coal Tar
Anti-Dandruff Shampoo

Fights Itchy, Flaky Scalp

Controls the symptoms of:

- psoriasis
- seborrheic dermatitis
- dandruff

Transparent formula
Gentle fragrance

Leaves hair shiny and manageable
With Coal Tar Topical Solution USP

8.5 FL OZ (251 mL)

05-2851A